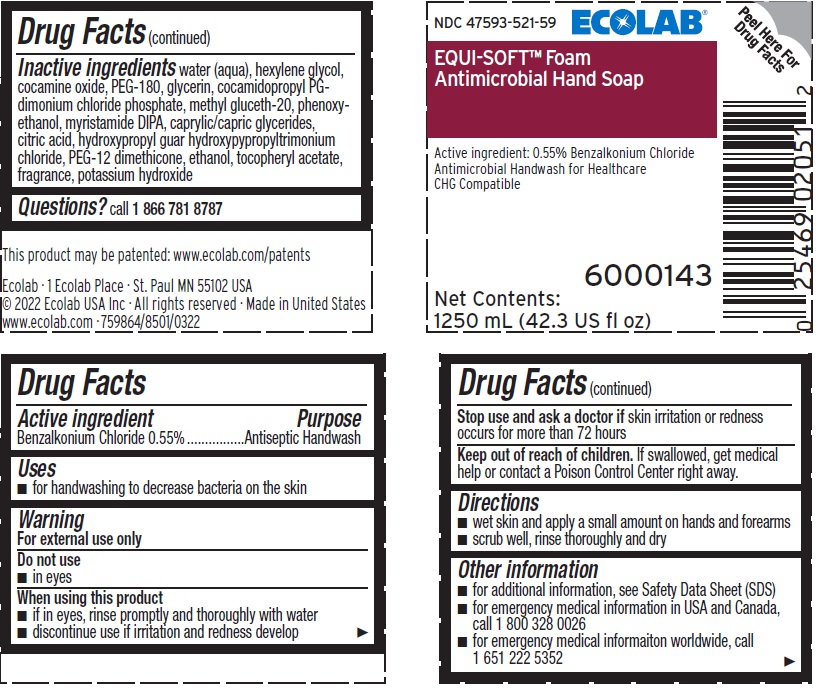 DRUG LABEL: Ecolab
NDC: 47593-521 | Form: SOLUTION
Manufacturer: Ecolab Inc.
Category: otc | Type: HUMAN OTC DRUG LABEL
Date: 20250404

ACTIVE INGREDIENTS: BENZALKONIUM CHLORIDE 5.5 mg/1 mL
INACTIVE INGREDIENTS: WATER; HEXYLENE GLYCOL; COCAMINE OXIDE; POLYETHYLENE GLYCOL 8000; GLYCERIN; COCAMIDOPROPYL PG-DIMONIUM CHLORIDE PHOSPHATE; METHYL GLUCETH-20; PHENOXYETHANOL; MYRISTIC DIISOPROPANOLAMIDE; GLYCERYL MONO- AND DICAPRYLOCAPRATE; ANHYDROUS CITRIC ACID; GUAR GUM; PEG-12 DIMETHICONE (300 CST); ALCOHOL; .ALPHA.-TOCOPHEROL ACETATE; POTASSIUM HYDROXIDE

Drug Facts

Purpose

Antiseptic handwash

Uses

- for handwashing to decrease bacteria on the skin

Warnings

- For external use only

Do not use

- In eyes

When using this product

- if in eyes, rinse promptly and thoroughly with water.
- discontinue use if irritation and redness develop.

Stop use and ask a doctor if skin irritation or redness occurs for more than 72 hours

Keep out of reach of children. If swallowed, get medical help or contact a Poison Control Center right away.

Directions

- wet skin and spread a small amount on hands and forearms
- scrub well, rinse thoroughly and dry

Other information

- for additional information, see Safety Data Sheet (SDS)
- for emergency medical information in USA and Canada, call 1 800 328 0026
- for emergency medical information worldwide, call 1 651 222 5352

Inactive ingredients

water (aqua), hexylene glycol, cocamine oxide, PEG-180, glycerin, cocamidopropyl PG-dimonium chloride phosphate, methyl gluceth-20, phenoxyethanol, myristamide DIPA, caprylic/capric glycerides, citric acid, hydroxypropyl guar hydroxypypropyltrimonium chloride, PEG-12 dimethicone, ethanol, tocopheryl acetate, fragrance, potassium hydroxide

Questions? call 1 866 781 8787

Representative Label and Principal Display Panel

47593-521-59

ECOLAB®

EQUI-SOFT™ Foam

ANTIMICROBIAL HAND SOAP

Active Ingredient: 0.55% Benzalkonium Chloride

Antimicrobial Handwash for Healthcare

CHG Compatible

6000143

1250 mL (42.3 US fl oz)

Ecolab · 1 Ecolab Place · St. Paul MN 55102 USA

© 2022 Ecolab USA Inc · All rights reserved · Made in United States

www.ecolab.com · 759864/8501/0322